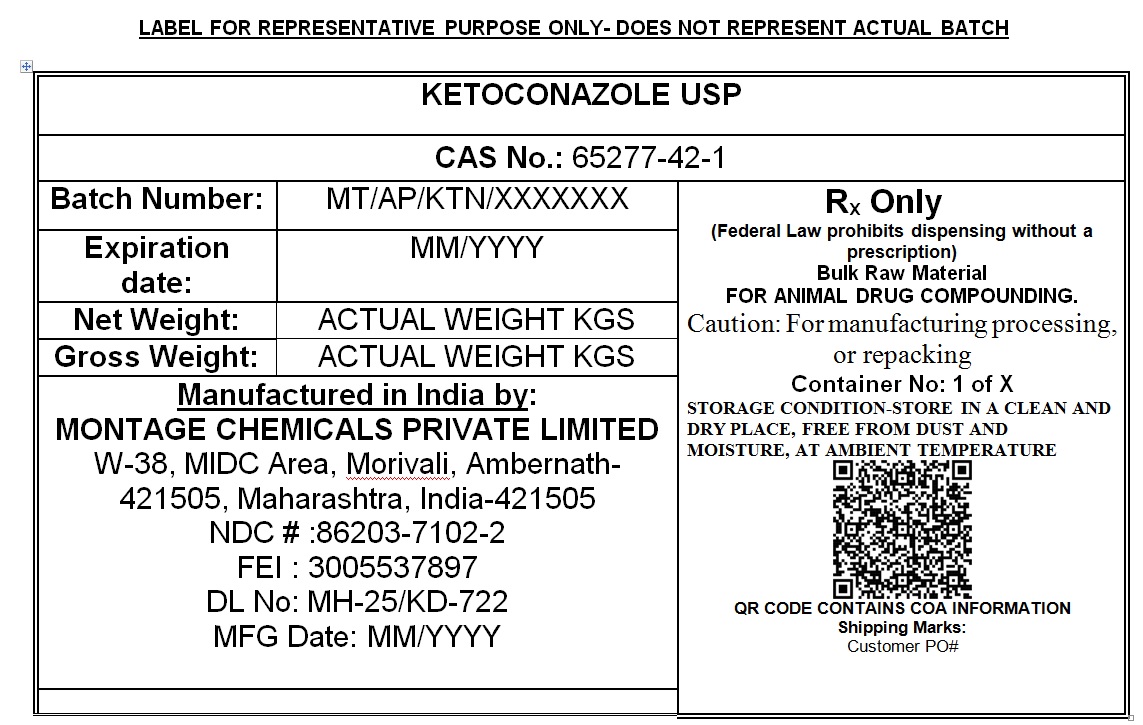 DRUG LABEL: KETOCONAZOLE
NDC: 86203-7102 | Form: POWDER
Manufacturer: MONTAGE CHEMICALS PRIVATE LIMITED
Category: other | Type: BULK INGREDIENT - ANIMAL DRUG
Date: 20260114

ACTIVE INGREDIENTS: KETOCONAZOLE 25 kg/25 kg

KETOCONAZOLE USP

PACKAGE LABEL

KETOCONAZOLE USP